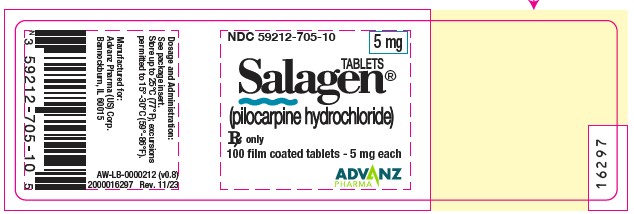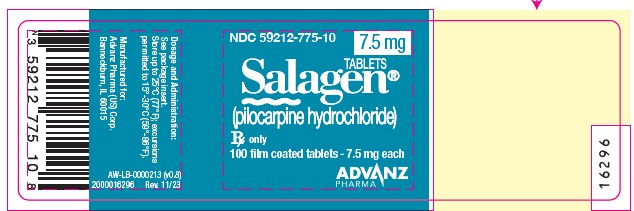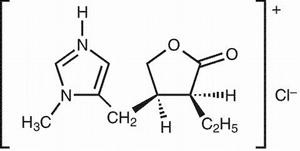 DRUG LABEL: Salagen
NDC: 59212-705 | Form: TABLET, FILM COATED
Manufacturer: Advanz Pharma (US) Corp.
Category: prescription | Type: Human Prescription Drug Label
Date: 20241205

ACTIVE INGREDIENTS: PILOCARPINE HYDROCHLORIDE 5 mg/1 1
INACTIVE INGREDIENTS: MICROCRYSTALLINE CELLULOSE; STEARIC ACID; HYPROMELLOSE, UNSPECIFIED; TITANIUM DIOXIDE; CARNAUBA WAX; POLYETHYLENE GLYCOL, UNSPECIFIED

SALAGEN
Tablets
(pilocarpine hydrochloride)

DESCRIPTION

SALAGEN® Tablets contain pilocarpine hydrochloride, a cholinergic agonist for oral use. Pilocarpine hydrochloride is a hygroscopic, odorless, bitter tasting white crystal or powder which is soluble in water and alcohol and virtually insoluble in most non-polar solvents. Pilocarpine hydrochloride, with a chemical name of (3S-cis)-2(3H)-Furanone, 3-ethyl-dihydro-4-[(1-methyl-1H-imidazol-5-yl)methyl] mono-hydrochloride, has a molecular weight of 244.72.

Each 5 mg SALAGEN® Tablet for oral administration contains 5 mg of pilocarpine hydrochloride. Inactive ingredients in the tablet, the tablet’s film coating, and polishing are: carnauba wax, hypromellose, microcrystalline cellulose, stearic acid, titanium dioxide and other ingredients.
Each 7.5 mg SALAGEN® Tablet for oral administration contains 7.5 mg of pilocarpine hydrochloride. Inactive ingredients in the tablet, the tablet’s film coating, and polishing are: carnauba wax, hypromellose, microcrystalline cellulose, stearic acid, titanium dioxide, FD&C blue#2 aluminum lake, and other ingredients.

CLINICAL PHARMACOLOGY

Pharmacodynamics:

Pilocarpine is a cholinergic parasympathomimetic agent exerting a broad spectrum of pharmacologic effects with predominant muscarinic action. Pilocarpine, in appropriate dosage, can increase secretion by the exocrine glands. The sweat, salivary, lacrimal, gastric, pancreatic, and intestinal glands and the mucous cells of the respiratory tract may be stimulated. When applied topically to the eye as a single dose it causes miosis, spasm of accommodation, and may cause a transitory rise in intraocular pressure followed by a more persistent fall. Dose-related smooth muscle stimulation of the intestinal tract may cause increased tone, increased motility, spasm, and tenesmus. Bronchial smooth muscle tone may increase. The tone and motility of urinary tract, gallbladder, and biliary duct smooth muscle may be enhanced. Pilocarpine may have paradoxical effects on the cardiovascular system. The expected effect of a muscarinic agonist is vasodepression, but administration of pilocarpine may produce hypertension after a brief episode of hypotension. Bradycardia and tachycardia have both been reported with use of pilocarpine.
In a study of 12 healthy male volunteers there was a dose-related increase in unstimulated salivary flow following single 5 and 10 mg oral doses of SALAGEN® Tablets. This effect of pilocarpine on salivary flow was time-related with an onset at 20 minutes and a peak effect at 1 hour with a duration of 3 to 5 hours (See Pharmacokinetics section).
Head & Neck Cancer Patients: In a 12 week randomized, double-blind, placebo-controlled study in 207 patients (placebo, N=65; 5 mg, N=73; 10 mg, N=69), increases from baseline (means 0.072 and 0.112 mL/min, ranges -0.690 to 0.728 and -0.380 to 1.689) of whole saliva flow for the 5 mg (63%) and 10 mg (90%) tablet, respectively, were seen 1 hour after the first dose of SALAGEN® Tablets. Increases in unstimulated parotid flow were seen following the first dose (means 0.025 and 0.046 mL/min, ranges 0 to 0.414 and -0.070 to 1.002 mL/min for the 5 and 10 mg dose, respectively). In this study, no correlation existed between the amount of increase in salivary flow and the degree of symptomatic relief.
Sjogren's Syndrome Patients: In two 12 week randomized, double-blind, placebo-controlled studies in 629 patients (placebo, N=253; 2.5 mg, N=121; 5 mg, N=255; 5-7.5 mg, N=114), the ability of SALAGEN® Tablets to stimulate saliva production was assessed. In these trials using varying doses of SALAGEN® Tablets (2.5-7.5 mg), the rate of saliva production was plotted against time. An Area Under the Curve (AUC) representing the total amount of saliva produced during the observation interval was calculated. Relative to placebo, an increase in the amount of saliva being produced was observed following the first dose of SALAGEN® Tablets and was maintained throughout the duration (12 weeks) of the trials in an approximate dose response fashion (See Clinical Studies section).

Pharmacokinetics:

In a multiple-dose pharmacokinetic study in male volunteers following 2 days of 5 or 10 mg of oral pilocarpine hydrochloride tablets given at 8 a.m., noontime, and 6 p.m., the mean elimination half-life was 0.76 hours for the 5 mg dose and 1.35 hours for the 10 mg dose. Tmax values were 1.25 hours and 0.85 hours. Cmax values were 15 ng/mL and 41 ng/mL. The AUC trapezoidal values were 33 h(ng/mL) and 108 h(ng/mL), respectively, for the 5 and 10 mg doses following the last 6 hour dose.
Pharmacokinetics in elderly male volunteers (N=11) were comparable to those in younger men. In five healthy elderly female volunteers, the mean Cmax and AUC were approximately twice that of elderly males and young normal male volunteers.
When taken with a high fat meal by 12 healthy male volunteers, there was a decrease in the rate of absorption of pilocarpine from SALAGEN® Tablets. Mean Tmax's were 1.47 and 0.87 hours, and mean Cmax's were 51.8 and 59.2 ng/mL for fed and fasted, respectively.
Limited information is available about the metabolism and elimination of pilocarpine in humans. Inactivation of pilocarpine is thought to occur at neuronal synapses and probably in plasma. Pilocarpine and its minimally active or inactive degradation products, including pilocarpic acid, are excreted in the urine. Pilocarpine does not bind to human or rat plasma proteins over a concentration range of 5 to 25,000 ng/mL. The effect of pilocarpine on plasma protein binding of other drugs has not been evaluated.
In patients with mild to moderate hepatic impairment (N=12), administration of a single 5 mg dose resulted in a 30% decrease in total plasma clearance and a doubling of exposure (as measured by AUC). Peak plasma levels were also increased by about 30% and half-life was increased to 2.1 hrs.
There were no significant differences in the pharmacokinetics of oral pilocarpine in volunteer subjects (N=8) with renal insufficiency (mean creatinine clearances 25.4 mL/min; range 9.8 - 40.8 mL/min) compared to the pharmacokinetics previously observed in normal volunteers.

CLINICAL STUDIES

Head & Neck Cancer Patients: A 12 week randomized, double-blind, placebo-controlled study in 207 patients (142 men, 65 women) was conducted in patients whose mean age was 58.5 years with a range of 19 to 77; the racial distribution was Caucasian 95%, Black 4%, and other 1%. In this population, a statistically significant improvement in mouth dryness occurred in the 5 and 10 mg SALAGEN® Tablet treated patients compared to placebo treated patients. The 5 and 10 mg treated patients could not be distinguished. (See Pharmacodynamics section for flow study details.)
Another 12 week, double-blind, randomized, placebo-controlled study was conducted in 162 patients whose mean age was 57.8 years with a range of 27 to 80; the racial distribution was Caucasian 88%, Black 10%, and other 2%. The effects of placebo were compared to 2.5 mg three times a day of SALAGEN® Tablets for 4 weeks followed by adjustment to 5 mg three times a day and 10 mg three times a day. Lowering of the dose was necessary because of adverse events in 3 of 67 patients treated with 5 mg of SALAGEN® Tablets and in 7 of 66 patients treated with 10 mg of SALAGEN® Tablets. After 4 weeks of treatment, 2.5 mg of SALAGEN® Tablets three times a day was comparable to placebo in relieving dryness. In patients treated with 5 mg and 10 mg of SALAGEN® Tablets, the greatest improvement in dryness was noted in patients with no measurable salivary flow at baseline.
In both studies, some patients noted improvement in the global assessment of their dry mouth, speaking without liquids, and a reduced need for supplemental oral comfort agents.
In the two placebo-controlled clinical trials, the most common adverse events related to drug, and increasing in rate as dose increases, were sweating, nausea, rhinitis, diarrhea, chills, flushing, urinary frequency, dizziness, and asthenia. The most common adverse experience causing withdrawal from treatment was sweating (5 mg t.i.d. ≤1%; 10 mg t.i.d. =12%).
Sjogren's Syndrome Patients: Two separate studies were conducted in patients with primary or secondary Sjogren's Syndrome. In both studies, the majority of patients best fit the European criteria for having primary Sjogren's Syndrome. ["Criteria for the Classification of Sjogren's Syndrome" (Vitali C, Bombardieri S, Moutsopoulos HM, et al: Preliminary criteria for the classification of Sjogren's Syndrome. Arthritis Rheum. 1993; 36:340-347.)]
A 12-week, randomized, double-blind, parallel-group, placebo-controlled study was conducted in 256 patients (14 men, 242 women) whose mean age was 57 years with a range of 24 to 85 years. The racial distribution was as follows: Caucasian 91%, Black 6%, and other 3%.
The effects of placebo were compared with those of SALAGEN® Tablets 5 mg four times a day (20 mg/day) for 6 weeks. At 6 weeks, the patients' dosage was increased from 5 mg SALAGEN® Tablets q.i.d. to 7.5 mg q.i.d. The data collected during the first 6 weeks of the trial were evaluated for safety and efficacy, and the data of the second 6 weeks of the trial were used to provide additional evidence of safety.
After 6 weeks of treatment, statistically significant global improvement of dry mouth was observed compared to placebo. "Global improvement" is defined as a score of 55 mm or more on a 100 mm visual analogue scale in response to the question, "Please rate your present condition of dry mouth (xerostomia) compared with your condition at the start of this study. Consider the changes to your dry mouth and other symptoms related to your dry mouth that have occurred since you have taken this medication." Patients' assessments of specific dry mouth symptoms such as severity of dry mouth, mouth discomfort, ability to speak without water, ability to sleep without drinking water, ability to swallow food without drinking, and a decreased use of saliva substitutes were found to be consistent with the significant global improvement described.
Another 12 week randomized, double-blind, parallel-group, placebo-controlled study was conducted in 373 patients (16 men, 357 women) whose mean age was 55 years with a range of 21 to 84. The racial distribution was Caucasian 80%, Oriental 14%, Black 2%, and 4% of other origin. The treatment groups were 2.5 mg pilocarpine tablets, 5 mg SALAGEN® Tablets, and placebo. All treatments were administered on a four times a day regimen.
After 12 weeks of treatment, statistically significant global improvement of dry mouth was observed at a dose of 5 mg compared with placebo. The 2.5 mg (10 mg/day) group was not significantly different than placebo. However, a subgroup of patients with rheumatoid arthritis tended to improve in global assessments at both the 2.5 mg q.i.d. (9 patients) and 5 mg q.i.d. (16 patients) dose (10-20 mg/day). The clinical significance of this finding is unknown.
Patients' assessments of specific dry mouth symptoms such as severity of dry mouth, mouth discomfort, ability to sleep without drinking water, and decreased use of saliva substitutes were also found to be consistent with the significant global improvement described when measured after 6 weeks and 12 weeks of SALAGEN® Tablets use.

INDICATIONS & USAGE

SALAGEN® Tablets are indicated for 1) the treatment of symptoms of dry mouth from salivary gland hypofunction caused by radiotherapy for cancer of the head and neck; and 2) the treatment of symptoms of dry mouth in patients with Sjogren's Syndrome.

CONTRAINDICATIONS

SALAGEN® Tablets are contraindicated in patients with uncontrolled asthma, known hypersensitivity to pilocarpine, and when miosis is undesirable, e.g., in acute iritis and in narrow-angle (angle closure) glaucoma.

WARNINGS

Cardiovascular Disease: Patients with significant cardiovascular disease may be unable to compensate for transient changes in hemodynamics or rhythm induced by pilocarpine. Pulmonary edema has been reported as a complication of pilocarpine toxicity from high ocular doses given for acute angle-closure glaucoma. Pilocarpine should be administered with caution in and under close medical supervision of patients with significant cardiovascular disease.
Ocular: Ocular formulations of pilocarpine have been reported to cause visual blurring which may result in decreased visual acuity, especially at night and in patients with central lens changes, and to cause impairment of depth perception. Caution should be advised while driving at night or performing hazardous activities in reduced lighting.
Pulmonary Disease: Pilocarpine has been reported to increase airway resistance, bronchial smooth muscle tone, and bronchial secretions. Pilocarpine hydrochloride should be administered with caution to and under close medical supervision in patients with controlled asthma, chronic bronchitis, or chronic obstructive pulmonary disease requiring pharmacotherapy.

PRECAUTIONS

General

Pilocarpine toxicity is characterized by an exaggeration of its parasympathomimetic effects. These may include: headache, visual disturbance, lacrimation, sweating, respiratory distress, gastrointestinal spasm, nausea, vomiting, diarrhea, atrioventricular block, tachycardia, bradycardia, hypotension, hypertension, shock, mental confusion, cardiac arrhythmia, and tremors.
The dose-related cardiovascular pharmacologic effects of pilocarpine include hypotension, hypertension, bradycardia, and tachycardia.
Pilocarpine should be administered with caution to patients with known or suspected cholelithiasis or biliary tract disease. Contractions of the gallbladder or biliary smooth muscle could precipitate complications including cholecystitis, cholangitis, and biliary obstruction.
Pilocarpine may increase ureteral smooth muscle tone and could theoretically precipitate renal colic (or "ureteral reflux"), particularly in patients with nephrolithiasis.
Cholinergic agonists may have dose-related central nervous system effects. This should be considered when treating patients with underlying cognitive or psychiatric disturbances.
Hepatic Insufficiency: Based on decreased plasma clearance observed in patients with moderate hepatic impairment, the starting dose in these patients should be 5 mg twice daily, followed by adjustment based on therapeutic response and tolerability. Patients with mild hepatic insufficiency (Child-Pugh score of 5-6) do not require dosage reductions. To date, pharmacokinetic studies in subjects with severe hepatic impairment (Child-Pugh score of 10-15) have not been carried out. The use of pilocarpine in these patients is not recommended.
Child-Pugh Scoring System for Hepatic Impairment

Clinical and Biochemical Measurements | Points Scored for Increasing Abnormality
 | 1 | 2 | 3
Encephalopathy (grade)* | None | 1 and 2 | 3 and 4
Ascites | Absent | Slight | Moderate
Bilirubin (mg. per 100 mL) | 1-2 | 2-3 | >3
Albumin (g. per 100 mL) | 3-5 | 2.8-3.5 | <2.8
Prothrombin Time (sec. Prolonged) | 1-4 | 4-6 | >6
For Primary Biliary Cirrhosis:- Bilirubin (mg. per 100 mL) | 1-4 | 4-10 | >10

* According to grading of Trey C, Burns D, and Saunders S. Treatment of hepatic coma by exchange blood transfusion. N Engl J Med. 1966; 274:473-481.
Reference: Pugh RNH, Murray-Lyon IM, Dawson JL, Pietroni MC, Williams R. Transection of the oesophagus for bleeding oesophageal varices. Brit J Surg. 1973; 60:646-9

Information for Patients

Patients should be informed that pilocarpine may cause visual disturbances, especially at night, that could impair their ability to drive safely. If a patient sweats excessively while taking pilocarpine hydrochloride and cannot drink enough liquid, the patient should consult a physician. Dehydration may develop.

Drug Interactions

Pilocarpine should be administered with caution to patients taking beta-adrenergic antagonists because of the possibility of conduction disturbances. Drugs with parasympathomimetic effects administered concurrently with pilocarpine would be expected to result in additive pharmacologic effects. Pilocarpine might antagonize the anticholinergic effects of drugs used concomitantly. These effects should be considered when anticholinergic properties may be contributing to the therapeutic effect of concomitant medication (e.g., atropine, inhaled ipratropium). While no formal drug interaction studies have been performed, the following concomitant drugs were used in at least 10% of patients in either or both Sjogren's efficacy studies: acetylsalicylic acid, artificial tears, calcium, conjugated estrogens, hydroxychloroquine sulfate, ibuprofen, levothyroxine sodium, medroxyprogesterone acetate, methotrexate, multivitamins, naproxen, omeprazole, paracetamol, and prednisone.

Carcinogenesis, Mutagenesis, Impairment of Fertility

Lifetime oral carcinogenicity studies were conducted in CD-1 mice and Sprague-Dawley rats. Pilocarpine did not induce tumors in mice at any dosage studied (up to 30 mg/kg/day, which yielded a systemic exposure approximately 50 times larger than the maximum systemic exposure observed clinically). In rats, a dosage of 18 mg/kg/day, which yielded a systemic exposure approximately 100 times larger than the maximum systemic exposure observed clinically, resulted in a statistically significant increase in the incidence of benign pheochromocytomas in both males and females, and a statistically significant increase in the incidence of hepatocellular adenomas in female rats. The tumorigenicity observed in rats was observed only at a large multiple of the maximum labeled clinical dose, and may not be relevant to clinical use.
No evidence that pilocarpine has the potential to cause genetic toxicity was obtained in a series of studies that included: 1) bacterial assays (Salmonella and E. coli) for reverse gene mutations; 2) an in vitro chromosome aberration assay in a Chinese hamster ovary cell line; 3) an in vivo chromosome aberration assay (micronucleus test) in mice; and 4) a primary DNA damage assay (unscheduled DNA synthesis) in rat hepatocyte primary cultures.
Oral administration of pilocarpine to male and female rats at a dosage of 18 mg/kg/day, which yielded a systemic exposure approximately 100 times larger than the maximum systemic exposure observed clinically, resulted in impaired reproductive function, including reduced fertility, decreased sperm motility, and morphologic evidence of abnormal sperm. It is unclear whether the reduction in fertility was due to effects on male animals, female animals, or both males and females. In dogs, exposure to pilocarpine at a dosage of 3 mg/kg/day (approximately 3 times the maximum recommended human dose when compared on the basis of body surface area (mg/m^2) estimates) for six months resulted in evidence of impaired spermatogenesis. The data obtained in these studies suggest that pilocarpine may impair the fertility of male and female humans. SALAGEN® Tablets should be administered to individuals who are attempting to conceive a child only if the potential benefit justifies potential impairment of fertility.

Pregnancy: Teratogenic Effects

Pilocarpine was associated with a reduction in the mean fetal body weight and an increase in the incidence of skeletal variations when given to pregnant rats at a dosage of 90 mg/kg/day (approximately 26 times the maximum recommended dose for a 50 kg human when compared on the basis of body surface area (mg/m^2) estimates). These effects may have been secondary to maternal toxicity. In another study, oral administration of pilocarpine to female rats during gestation and lactation at a dosage of 36 mg/kg/day (approximately 10 times the maximum recommended dose for a 50 kg human when compared on the basis of body surface area (mg/m^2) estimates) resulted in an increased incidence of stillbirths; decreased neonatal survival and reduced mean body weight of pups were observed at dosages of 18 mg/kg/day (approximately 5 times the maximum recommended dose for a 50 kg human when compared on the basis of body surface area (mg/m^2) estimates) and above. There are no adequate and well-controlled studies in pregnant women. SALAGEN® Tablets should be used during pregnancy only if the potential benefit justifies the potential risk to the fetus.

Nursing Mothers

It is not known whether this drug is excreted in human milk. Because many drugs are excreted in human milk and because of the potential for serious adverse reactions in nursing infants from SALAGEN® Tablets, a decision should be made whether to discontinue nursing or to discontinue the drug, taking into account the importance of the drug to the mother.

Pediatric Use

Safety and effectiveness in pediatric patients have not been established.

Geriatric Use

Head & Neck Cancer Patients: In the placebo-controlled clinical trials (See Clinical Studies section) the mean age of patients was approximately 58 years (range 19 to 80). Of these patients, 97/369 (61/217 receiving pilocarpine) were over the age of 65 years. In the healthy volunteer studies, 15/150 subjects were over the age of 65 years. In both study populations, the adverse events reported by those over 65 years and those 65 years and younger were comparable. Of the 15 elderly volunteers (5 women, 10 men), the 5 women had higher Cmax's and AUC's than the men. (See Pharmacokinetics section.)
Sjogren's Syndrome Patients: In the placebo-controlled clinical trials (See Clinical Studies section), the mean age of patients was approximately 55 years (range 21 to 85). The adverse events reported by those over 65 years and those 65 years and younger were comparable except for notable trends for urinary frequency, diarrhea, and dizziness (See ADVERSE REACTIONS section).

ADVERSE REACTIONS

Head & Neck Cancer Patients: In controlled studies, 217 patients received pilocarpine, of whom 68% were men and 32% were women. Race distribution was 91% Caucasian, 8% Black, and 1% of other origin. Mean age was approximately 58 years. The majority of patients were between 50 and 64 years (51%), 33% were 65 years and older and 16% were younger than 50 years of age. The most frequent adverse experiences associated with SALAGEN® Tablets were a consequence of the expected pharmacologic effects of pilocarpine.

Adverse Event | Pilocarpine HCl |  | Placebo
 | 10 mg t.i.d. (30 mg/day) | 5 mg t.i.d. (15 mg/day) | (t.i.d.)
Sweating | N = 121/68% | N = 141/29% | N = 152/9%
Nausea | 15 | 6 | 4
Rhinitis | 14 | 5 | 7
Diarrhea | 7 | 4 | 5
Chills | 15 | 3 | <1
Flushing | 13 | 8 | 3
Urinary Frequency | 12 | 9 | 7
Dizziness | 12 | 5 | 4
Asthenia | 12 | 6 | 3

In addition, the following adverse events (≥3% incidence) were reported at dosages of 15-30 mg/day in the controlled clinical trials:

Adverse Event | Pilocarpine HCl | Placebo
 | 5-10 mg t.i.d. (15-30 mg/day) | (t.i.d.)
Headache | N = 212/11% | N = 152/8%
Dyspepsia | 7 | 5
Lacrimation | 6 | 8
Edema | 5 | 4
Abdominal Pain | 4 | 4
Amblyopia | 4 | 2
Vomiting | 4 | 1
Pharyngitis | 3 | 8
Hypertension | 3 | 1

The following events were reported with treated head and neck cancer patients at incidences of 1% to 2% at dosages of 7.5 to 30 mg/day: abnormal vision, conjunctivitis, dysphagia, epistaxis, myalgias, pruritus, rash, sinusitis, tachycardia, taste perversion, tremor, voice alteration.
The following events were reported rarely in treated head and neck cancer patients (<1%): Causal relation is unknown.
Body as a whole: body odor, hypothermia, mucous membrane abnormality
Cardiovascular: bradycardia, ECG abnormality, palpitations, syncope
Digestive: anorexia, increased appetite, esophagitis, gastrointestinal disorder, tongue disorder
Hematologic: leukopenia, lymphadenopathy
Nervous: anxiety, confusion, depression, abnormal dreams, hyperkinesia, hypesthesia, nervousness, parethesias, speech disorder, twitching
Respiratory: increased sputum, stridor, yawning
Skin: seborrhea
Special senses: deafness, eye pain, glaucoma
Urogenital: dysuria, metrorrhagia, urinary impairment
In long-term treatment were two patients with underlying cardiovascular disease of whom one experienced a myocardial infarct and another an episode of syncope. The association with drug is uncertain.

Sjogren's Syndrome Patients: In controlled studies, 376 patients received pilocarpine, of whom 5% were men and 95% were women. Race distribution was 84% Caucasian, 9% Oriental, 3% Black, and 4% of other origin. Mean age was 55 years. The majority of patients were between 40 and 69 years (70%), 16% were 70 years and older and 14% were younger than 40 years of age. Of these patients, 161/629 (89/376 receiving pilocarpine) were over the age of 65 years. The adverse events reported by those over 65 years and those 65 years and younger were comparable except for notable trends for urinary frequency, diarrhea, and dizziness. The incidences of urinary frequency and diarrhea in the elderly were about double those of the non-elderly. The incidence of dizziness was about three times as high in the elderly as in the non-elderly. These adverse experiences were not considered to be serious. In the 2 placebo-controlled studies, the most common adverse events related to drug use were sweating, urinary frequency, chills, and vasodilatation (flushing). The most commonly reported reason for patient discontinuation of treatment was sweating. Expected pharmacologic effects of pilocarpine include the following adverse experiences associated with SALAGEN® Tablets:

Adverse Event | Pilocarpine HCl | Placebo
 | 5 mg q.i.d. (20 mg/day) | (q.i.d.)
Sweating | N = 255/40% | N = 253/7%
Urinary Frequency | 10 | 4
Nausea | 9 | 9
Flushing | 9 | 2
Rhinitis | 7 | 8
Diarrhea | 6 | 7
Chills | 4 | 2
Increased Salivation | 3 | 0
Asthenia | 2 | 2

In addition, the following adverse events (≥3% incidence) were reported at dosages of 20 mg/day in the controlled clinical trials:

Adverse Event | Pilocarpine HCl | Placebo
 | 5 mg q.i.d. (20 mg/day) | (q.i.d.)
Headache | N = 255/13% | N = 253/19%
Flu Syndrome | 9 | 9
Dyspepsia | 7 | 7
Dizziness | 6 | 7
Pain | 4 | 2
Sinusitis | 4 | 5
Abdominal Pain | 3 | 4
Vomiting | 3 | 1
Pharyngitis | 2 | 5
Rash | 2 | 3
Infection | 2 | 6

The following events were reported in Sjogren's patients at incidences of 1% to 2% at dosing of 20 mg/day: accidental injury, allergic reaction, back pain, blurred vision, constipation, increased cough, edema, epistaxis, face edema, fever, flatulence, glossitis, lab test abnormalities, including chemistry, hematology, and urinalysis, myalgia, palpitation, pruritus, somnolence, stomatitis, tachycardia, tinnitus, urinary incontinence, urinary tract infection, and vaginitis.
The following events were reported rarely in treated Sjogren's patients (<1%) at dosing of 10-30 mg/day: Causal relation is unknown.
Body as a whole: chest pain, cyst, death, moniliasis, neck pain, neck rigidity, photosensitivity reaction
Cardiovascular: angina pectoris, arrhythmia, ECG abnormality, hypotension, hypertension, intracranial hemorrhage, migraine, myocardial infarction
Digestive: anorexia, bilirubinemia, cholelithiasis, colitis, dry mouth, eructation, gastritis, gastroenteritis, gastrointestinal disorder, gingivitis, hepatitis, abnormal liver function tests, melena, nausea & vomiting, pancreatitis, parotid gland enlargement, salivary gland enlargement, sputum increased, taste loss, tongue disorder, tooth disorder
Hematologic: hematuria, lymphadenopathy, abnormal platelets, thrombocythemia, thrombocytopenia, thrombosis, abnormal WBC
Metabolic and Nutritional: peripheral edema, hypoglycemia
Musculoskeletal: arthralgia, arthritis, bone disorder, spontaneous bone fracture, pathological fracture, myasthenia, tendon disorder, tenosynovitis
Nervous: aphasia, confusion, depression, abnormal dreams, emotional lability, hyperkinesia, hypesthesia, insomnia, leg cramps, nervousness, parethesias, abnormal thinking, tremor
Respiratory: bronchitis, dyspnea, hiccup, laryngismus, laryngitis, pneumonia, viral infection, voice alteration
Skin: alopecia, contact dermatitis, dry skin, eczema, erythema nodosum, exfoliative dermatitis, herpes simplex, skin ulcer, vesiculobullous rash
Special Senses: cataract, conjunctivitis, dry eyes, ear disorder, ear pain, eye disorder, eye hemorrhage, glaucoma, lacrimation disorder, retinal disorder, taste perversion, abnormal vision
Urogenital: breast pain, dysuria, mastitis, menorrhagia, metrorrhagia, ovarian disorder, pyuria, salpingitis, urethral pain, urinary urgency, vaginal hemorrhage, vaginal moniliasis
The following adverse experiences have been reported rarely with ocular pilocarpine: A-V block, agitation, ciliary congestion, confusion, delusion, depression, dermatitis, middle ear disturbance, eyelid twitching, malignant glaucoma, iris cysts, macular hole, shock, and visual hallucination.

To report SUSPECTED ADVERSE REACTIONS, contact Advanz Pharma (US) Corp. at 1-877-370-1142 or FDA at 1-800-FDA-1088 or www.fda.gov/medwatch

MANAGEMENT OF OVERDOSE

Fatal overdosage with pilocarpine has been reported in the scientific literature at doses presumed to be greater than 100 mg in two hospitalized patients. 100 mg of pilocarpine is considered potentially fatal. Overdosage should be treated with atropine titration (0.5 mg to 1.0 mg given subcutaneously or intravenously) and supportive measures to maintain respiration and circulation. Epinephrine (0.3 mg to 1.0 mg, subcutaneously or intramuscularly) may also be of value in the presence of severe cardiovascular depression or bronchoconstriction. It is not known if pilocarpine is dialyzable.

DOSAGE AND ADMINISTRATION

Regardless of the indication, the starting dose in patients with moderate hepatic impairment should be 5 mg twice daily, followed by adjustment based on therapeutic response and tolerability. Patients with mild hepatic insufficiency do not require dosage reductions. The use of pilocarpine in patients with severe hepatic insufficiency is not recommended. If needed, refer to the Hepatic Insufficiency subsection of the Precautions section of this label for definitions of mild, moderate and severe hepatic impairment.
Head & Neck Cancer Patients: The recommended initial dose of SALAGEN® Tablets is 5 mg taken three times a day. Dosage should be titrated according to therapeutic response and tolerance. The usual dosage range is up to 15-30 mg per day. (Not to exceed 10 mg per dose.) Although early improvement may be realized, at least 12 weeks of uninterrupted therapy with SALAGEN® Tablets may be necessary to assess whether a beneficial response will be achieved. The incidence of the most common adverse events increases with dose. The lowest dose that is tolerated and effective should be used for maintenance.
Sjogren's Syndrome Patients: The recommended dose of SALAGEN® Tablets is 5 mg taken four times a day. Efficacy was established by 6 weeks of use.

HOW SUPPLIED

SALAGEN® Tablets, 5 mg, are white, film coated, debossed round tablets, coded SAL 5. Each tablet contains 5 mg pilocarpine hydrochloride. They are supplied as follows: NDC 59212-705-10 bottles of 100
Store up to 25°C (77°F); excursions permitted to 15°-30°C (59°-86°F).
SALAGEN® Tablets, 7.5 mg, are blue, film coated, debossed round tablets, coded SAL 7.5. Each tablet contains 7.5 mg pilocarpine hydrochloride. They are supplied as follows: NDC 59212-775-10 bottles of 100
Store up to 25°C (77°F); excursions permitted to 15°-30°C (59°-86°F).

Manufactured for:
Advanz Pharma (US) Corp.
Bannockburn, IL 60015

Nov 2023

SALAGEN® is a registered trademark of Mercury Pharma Group Limited. Distributed by Advanz Pharma (US) Corp. under license.

PRINCIPAL DISPLAY PANEL

NDA 59212-705-10 5 mg

SALAGEN® Tablets(pilocarpine hydrochloride)
Rx only
100 film coated tablets - 5 mg each
ADVANZ PHARMA

PRINCIPAL DISPLAY PANEL

NDA 59212-775-10 7.5 mg
SALAGEN® Tablets(pilocarpine hydrochloride)
Rx only
100 film coated tablets - 7.5 mg each

ADVANZ PHARMA